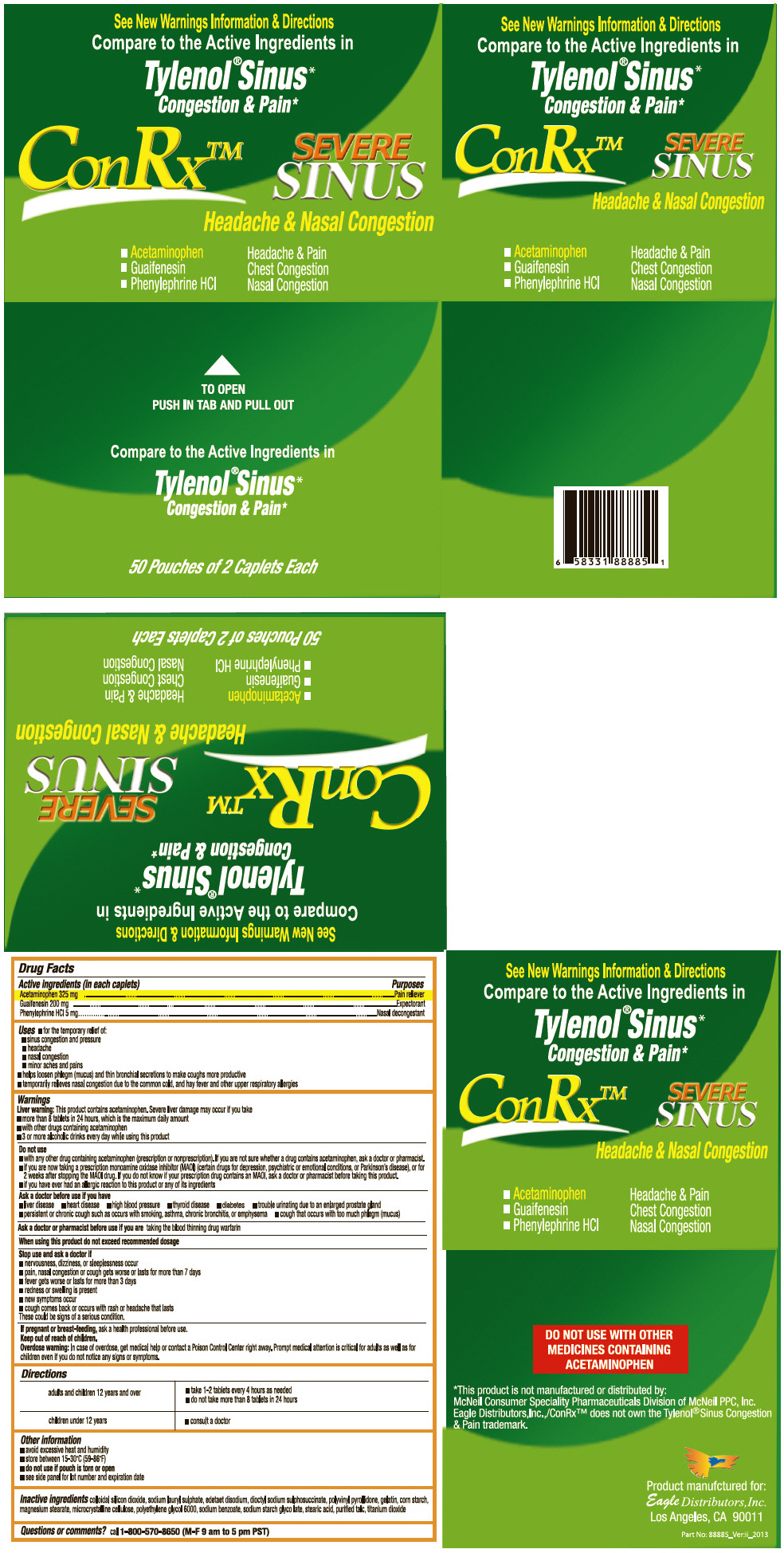 DRUG LABEL: ConRx Sinus
NDC: 68737-236 | Form: TABLET
Manufacturer: Eagle Distributors,Inc.
Category: otc | Type: HUMAN OTC DRUG LABEL
Date: 20130211

ACTIVE INGREDIENTS: Acetaminophen 325 mg/1 1; Guaifenesin 200 mg/1 1; Phenylephrine Hydrochloride 5 mg/1 1
INACTIVE INGREDIENTS: SILICON DIOXIDE; SODIUM LAURYL SULFATE; EDETATE DISODIUM; BIS(1-METHYLAMYL) SODIUM SULFOSUCCINATE; STARCH, CORN; POVIDONE K90; GELATIN; MAGNESIUM STEARATE; CELLULOSE, MICROCRYSTALLINE; POLYETHYLENE GLYCOL 6000; SODIUM BENZOATE; SODIUM STARCH GLYCOLATE TYPE A CORN; STEARIC ACID; TALC; TITANIUM DIOXIDE

ConRx™ Sinus

Active ingredient (in each tablet)

Acetaminophen 325mg

Guaifenesin 200mg

Phenylephrine HCl 5mg

Purpose

Pain reliever/ fever reducer

Expectorant

Nasal decongestant

Uses

Uses For the temporary relief of: sinus congestion and pressure, headache, nasal congestion, minor aches and pains, helps loosen phlegm (mucus) and thin bronchial secretions to make coughs more productive, temporarily relieves nasal congestion due to the common cold, and hay fever and other upper respiratory allergies.

Warnings

- Liver warning: This product contains acetaminophen. Severe liver damage may occur if you take: more than 8 tablets in 24 hours, which is the maximum daily amount for this product
- with other drugs containing acetaminophen
- 3 or more alcoholic drinks every day while using this product

Do not use

- with any other drug containing acetaminophen (prescription or nonprescription). If you are not sure whether a drug contains acetaminophen, ask a doctor or pharmacist.
- if you are now taking a prescription monoamine oxidase inhibitor (MAOI) (certain drugs for depression, psychiatric or emotional conditions, or Parkinson's disease), or for 2 weeks after stopping the MAOI drug. If you do not know if your prescription drug contains an MAOI, ask a doctor or pharmacist before taking this product.
- If you have ever had an allergic reaction to this product or any of its ingredients

Ask a doctor before use if you have

- liver disease
- heart disease
- high blood pressure
- thyroid disease
- diabetes
- trouble urinating due to an enlarged prostate gland
- a persistent chronic cough such as occurs with smoking, asthma, chronic bronchitis, or emphysema
- cough that occurs with too much phlegm (mucus)

Ask a doctor or pharmacist before use if you are

- taking the blood thinning drug warfarin

Stop use and ask a doctor if

- nervousness, dizziness, or sleeplessness occur
- pain, nasal congestion or cough gets worse or lasts for more than 7 days
- fever gets more than 3 days
- redness or swelling is present
- new symptoms occur
- cough comes back or occurs with rash or headache that lasts.
  These could be signs of serious conditions.

PREGNANCY OR BREAST FEEDING

If pregnant or breast-feeding, ask a health professional before use.

Keep out of reach of children.

Overdose warning

In case of overdose, get medical help or contact a Poison Center right away. Prompt medical attention is critical for adults as well as for children even if you do not notice any signs or symptoms.

Directions

Adults and Children 12 years and over | - Take 1-2 tablets every 4 hours as needed - Do not taking more than 8 tablets in 24 hour
Children under 12 years of age | Consult a doctor

Other Information

- Do not use if pouch is torn or damaged.
- Store between 15-30°C (59-86°F). Avoid excessive heat and humidity.
- See side panel for lot number and expiration date.

Inactive ingredients

Colloidal silicon dioxide, Sodium Lauryl Sulphate, Edetaet disodium, dioctyl sodium sulphosuccinate, polyvinyl pyrollidone, gelatin, corn starch', magnesium Stearate, microcrystalline cellulose, polyethylene glycol 6000,Sodium Benzoate ,Sodium Starch Glycolate, Stearic acid, Purified Talc, Titanium Dioxide.

PRINCIPAL DISPLAY PANEL - 2 Caplets × 50 Pouch Box

See New Warnings Information & Directions

Compare to the Active Ingredients in

Tylenol® Sinus*

Congestion & Pain*

ConRx™

SEVERE
SINUS

Headache & Nasal Congestion

- Acetaminophen
  Headache & Pain
- Guaifenesin
  Chest Congestion
- Phenylephrine HCl
  Nasal Congestion

TO OPEN
PUSH IN TAB AND PULL OUT

Compare to the Active Ingredients in

Tylenol® Sinus*
Congestion & Pain*

50 Pouches of 2 Caplets Each